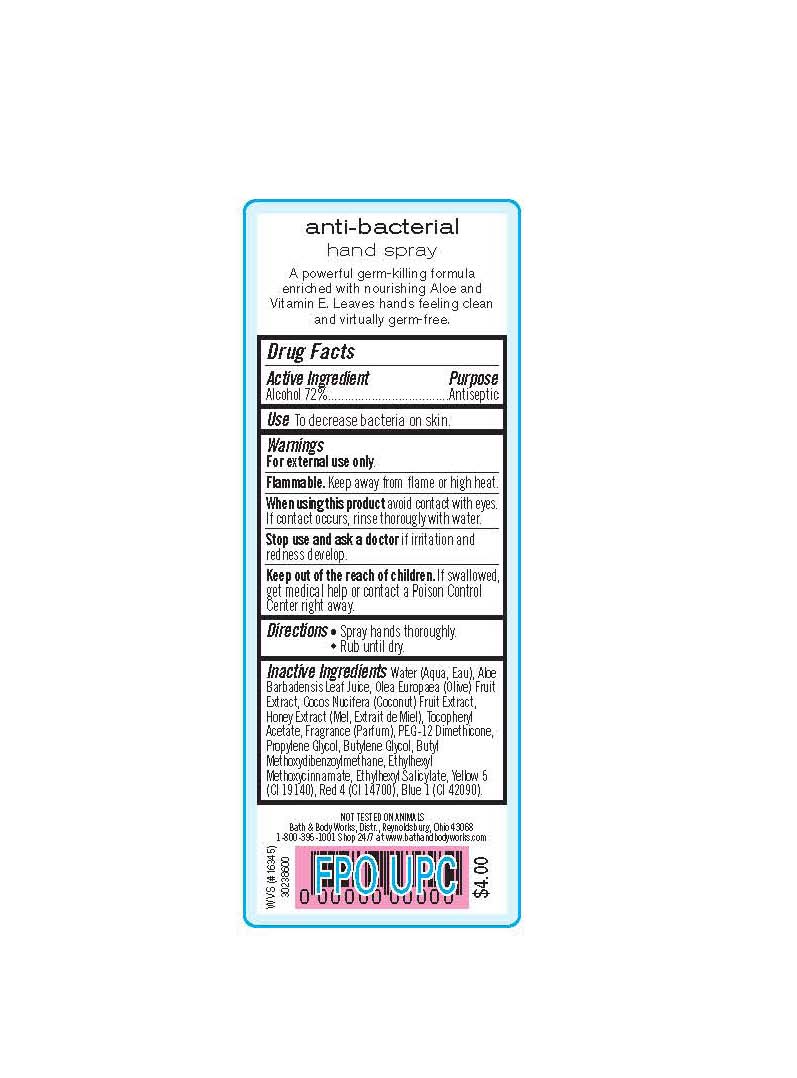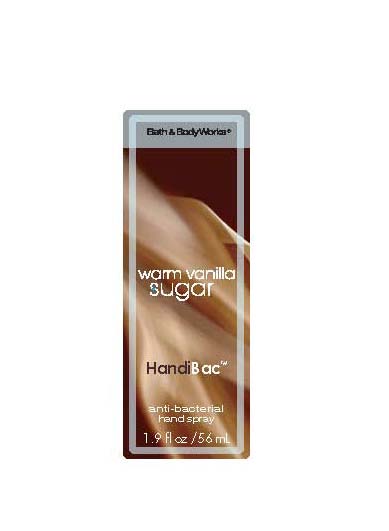 DRUG LABEL: Anti-Bacterial Hand Spray
NDC: 62670-3757 | Form: LIQUID
Manufacturer: Bath & Body Works, Inc.
Category: otc | Type: HUMAN OTC DRUG LABEL
Date: 20101221

ACTIVE INGREDIENTS: ALCOHOL 72 mL/100 mL
INACTIVE INGREDIENTS: WATER; ALOE VERA LEAF; BLACK OLIVE; COCONUT ; HONEY; .ALPHA.-TOCOPHEROL ACETATE, D-; DIMETHICONE; PROPYLENE GLYCOL; BUTYLENE GLYCOL; AVOBENZONE; OCTINOXATE; OCTISALATE; FD&C YELLOW NO. 5; FD&C RED NO. 4 ; FD&C BLUE NO. 1

DRUG FACTS

ACTIVE INGREDIENT

Alcohol (72%)

PURPOSE

Antiseptic

USE

To decrease bacteria on skin.

WARNINGS

For external use only.

FLAMMABLE

Keep away from flame or high heat.

WHEN USING THIS PRODUCT

avoid contact with eyes. If contact occurs, rinse thoroughly with water.

STOP USE AND ASK A DOCTOR

if irritation and redness develop.

KEEP OUT OF THE REACH OF CHILDREN

If swallowed, get medical help or contact a Poison Control Center right away.

DIRECTIONS

- Spray hands thoroughly.
- Rub until dry.

INACTIVE INGREDIENTS

Water (Aqua, Eau), Aloe Barbadensis Leaf Juice, Olea Europaea (Olive) Fruit Extract, Cocos Nucifera (Coconut) Fruit Extract, Honey Extract (Mel, Extrait de Miel), Tocopheryl Acetate, Fragrance (Parfum), PEG-12 Dimethicone, Propylene Glycol, Butylene Glycol, Butyl Methoxydibenzoylmethane, Ethylhexyl Methoxycinnamate, Ethylhexyl Salicylate, Yellow 5 (CI 19140), Red 4 (CI 14700), Blue 1 (CI 42090).

COMPANY INFORMATION

Bath & Body Works, Distr.
Reynoldsburg, Ohio 43068
1-800-395-1001
www.bathandbodyworks.com